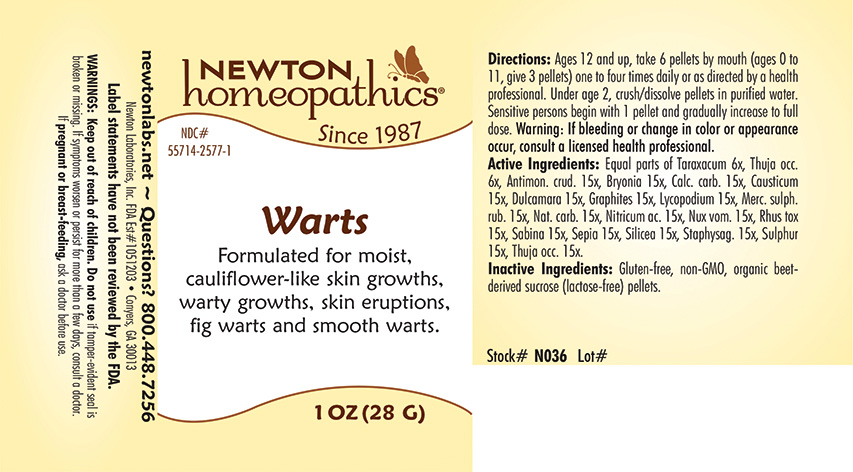 DRUG LABEL: Warts
NDC: 55714-2577 | Form: PELLET
Manufacturer: Newton Laboratories, Inc.
Category: homeopathic | Type: HUMAN OTC DRUG LABEL
Date: 20221219

ACTIVE INGREDIENTS: ANTIMONY TRISULFIDE 15 [hp_X]/1 g; BRYONIA ALBA ROOT 15 [hp_X]/1 g; OYSTER SHELL CALCIUM CARBONATE, CRUDE 15 [hp_X]/1 g; CAUSTICUM 15 [hp_X]/1 g; SOLANUM DULCAMARA TOP 15 [hp_X]/1 g; GRAPHITE 15 [hp_X]/1 g; LYCOPODIUM CLAVATUM SPORE 15 [hp_X]/1 g; MERCURIC SULFIDE 15 [hp_X]/1 g; SODIUM CARBONATE 15 [hp_X]/1 g; NITRIC ACID 15 [hp_X]/1 g; STRYCHNOS NUX-VOMICA SEED 15 [hp_X]/1 g; TOXICODENDRON PUBESCENS LEAF 15 [hp_X]/1 g; JUNIPERUS SABINA LEAFY TWIG 15 [hp_X]/1 g; SEPIA OFFICINALIS JUICE 15 [hp_X]/1 g; SILICON DIOXIDE 15 [hp_X]/1 g; DELPHINIUM STAPHISAGRIA SEED 15 [hp_X]/1 g; SULFUR 15 [hp_X]/1 g; THUJA OCCIDENTALIS LEAFY TWIG 15 [hp_X]/1 g; TARAXACUM OFFICINALE 6 [hp_X]/1 g
INACTIVE INGREDIENTS: SUCROSE

Warts 2577P

INDICATIONS & USAGE SECTION

Formulated for moist, cauliflower-like skin growths, warty growths, skin eruptions, fig warts and smooth warts.

DOSAGE & ADMINISTRATION SECTION

Directions: Ages 12 and up, take 6 pellets by mouth (ages 0 to 11, give 3 pellets) one to four times daily or as directed by a health professional. Under age 2, crush/dissolve pellets in purified water. Sensitive persons begins with 1 pellet and gradually increase to full dose. WARNING: If bleeding or change in color or appearance occur, consult a licensed health professional.

OTC - ACTIVE INGREDIENT SECTION

Equal parts of Taraxacum 6x, Thuja occ. 6x, Antimon. crud. 15x, Bryonia 15x, Calc.carb. 15x, Causticum 15x, Dulcamara 15x, Graphites 15x, Lycopodium 15x, Merc. sulph. rub. 15x, Nat. carb. 15x, Nitricum ac.15x, Nux vom. 15x, Rhus tox 15x, Sabina 15x, Sepia 15x, Silicea 15x, Staphysag. 15x, Sulphur 15x, Thuja occ. 15x.

OTC - PURPOSE SECTION

Formulated for moist, cauliflower-like skin growths, warty growths, skin eruptions, fig warts and smooth warts.

INACTIVE INGREDIENT SECTION

Inactive Ingredients: Gluten-free, non-GMO, organic beet-derived sucrose (lactose-free) pellets.

QUESTIONS SECTION

newtonlabs.net ~ Questions? 800.448.7256

Newton Laboratories, Inc. FDA Est # 1051203 - Conyers, GA 30013

WARNINGS SECTION

WARNINGS: If bleeding or change in color or appearance occur, consult a licensed health professional.

WARNINGS: Keep out of reach of children. Do not use if tamper-evident seal is broken or missing. If symptoms worsen or persist for more than a few days, consult a doctor. If pregnant or breast-feeding, ask a doctor before use.

OTC - PREGNANCY OR BREAST FEEDING SECTION

If pregnant or breast-feeding, ask a doctor before use.

OTC - KEEP OUT OF REACH OF CHILDREN SECTION

Keep out of reach of children.